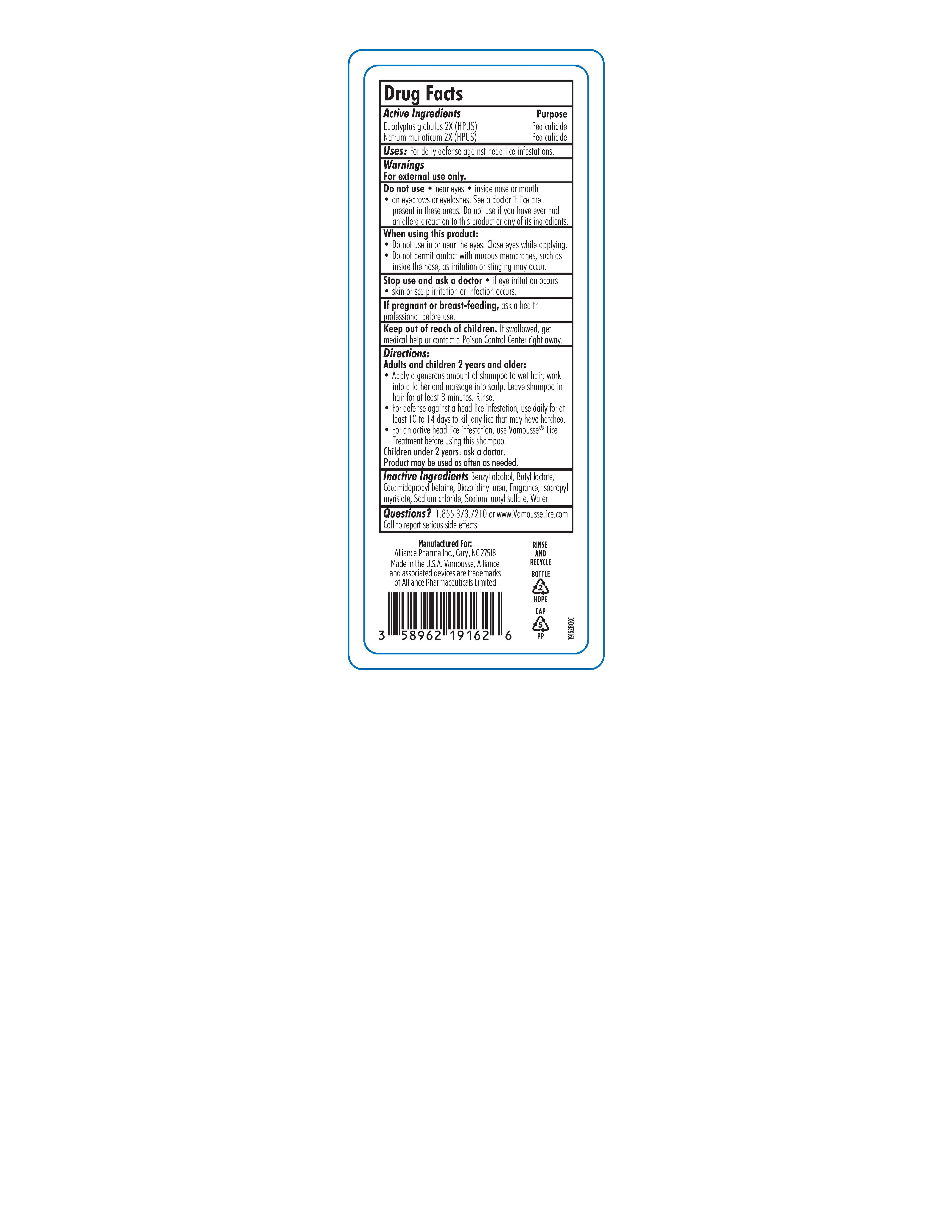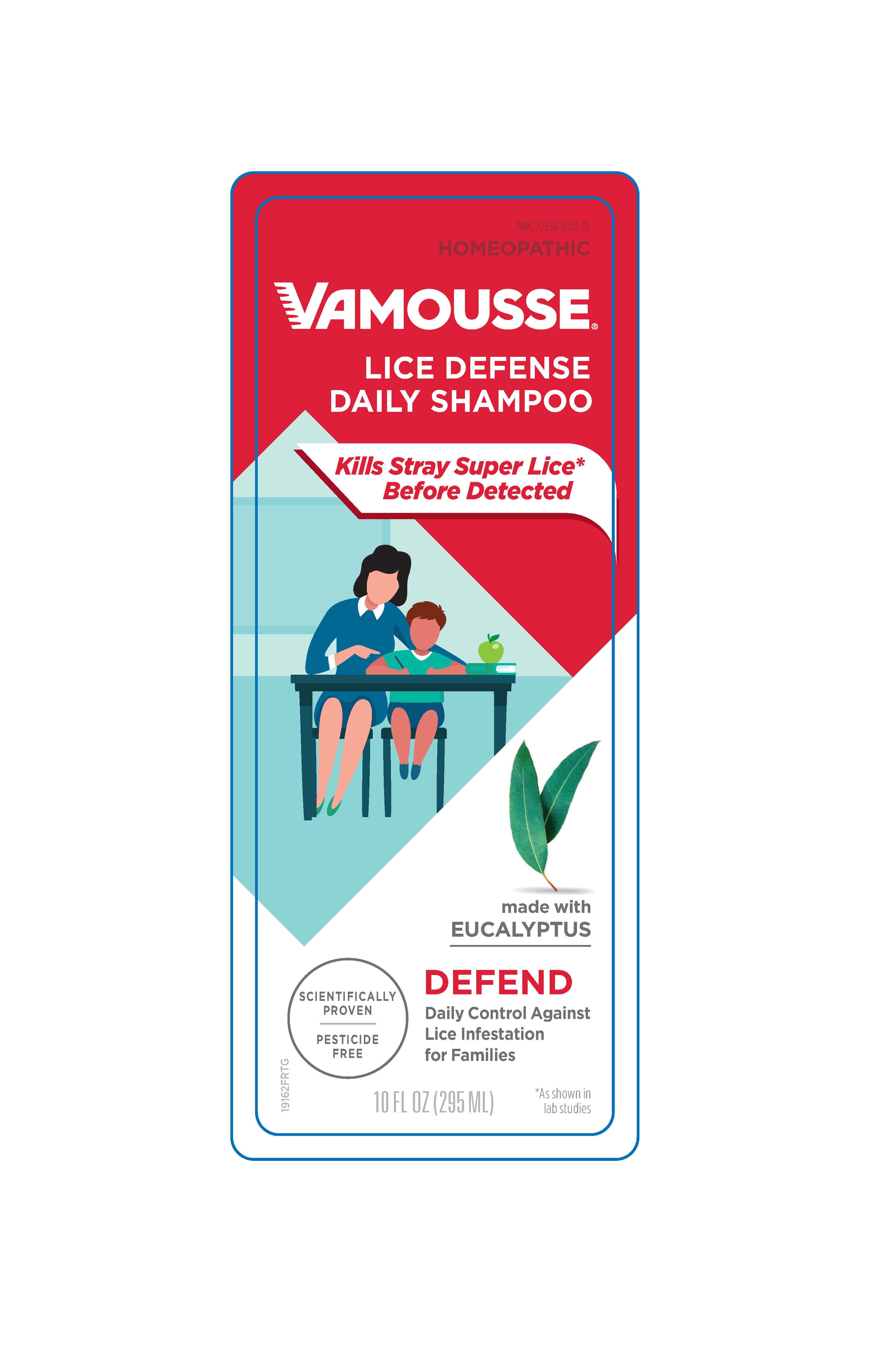 DRUG LABEL: Vamousse Lice Defense
NDC: 72238-002 | Form: SHAMPOO
Manufacturer: Alliance Pharma Inc.
Category: homeopathic | Type: HUMAN OTC DRUG LABEL
Date: 20230717

ACTIVE INGREDIENTS: EUCALYPTUS GLOBULUS LEAF 2 [hp_X]/1 mL; SODIUM CHLORIDE 2 [hp_X]/1 mL
INACTIVE INGREDIENTS: MENTHA ARVENSIS FLOWER OIL; EUCALYPTUS OIL; PEPPERMINT; DIAZOLIDINYL UREA; COCAMIDOPROPYL BETAINE; LINALOOL, (+/-)-; MENTHYL ACETATE, (-)-; OCTYL ACETATE; PEPPERMINT OIL; SODIUM LAURYL SULFATE; CARVONE, (-)-; ORANGE OIL; LIMONENE, (+)-; MENTHONE, (+/-)-; ISOPROPYL MYRISTATE; CITRAL; LEMON OIL; GERANYL ACETATE; SPEARMINT OIL; PENNYROYAL OIL; LEVOMENTHOL; WATER; DECANAL; CARYOPHYLLENE; DIPROPYLENE GLYCOL; LINALYL ACETATE, (+)-; BERGAMOT OIL; BENZYL ALCOHOL; .ALPHA.-TERPINEOL; BUTYL LACTATE

Lice Defense Shampoo 295ml/118ml

DRUG FACTS-Active Ingredients

Eucalyptus globulus 2X (HPUS)

Natrum muriaticum 2X (HPUS)

Purpose

Pediculicide

Uses

For daily defense against head lice infestations.

Warnings

For external use only.

Warnings

Do not use • near eyes • inside nose or mouth

• on eyebrows or eyelashes. See a doctor if lice are

present in these areas. Do not use if you have ever had an

allergic reaction to this product or any of its ingredients.

Warnings

When using this product:

• Do not use in or near the eyes. Close eyes while applying.

• Do not permit contact with mucous membranes, such as

inside the nose, as irritation or stinging may occur.

Warnings

Stop use and ask a doctor • if eye irritation occurs

• skin or scalp irritation or infection occurs.

Warnings

If pregnant or breast-feeding, ask a health

professional before use.

Children's Warning

Keep out of reach of children. If swallowed, get

medical help or contact a Poison Control Center right away.

Directions

Adults and children 2 years and older:

• Apply a generous amount of shampoo to wet hair, work

into a lather and massage into scalp. Leave shampoo in

hair for at least 3 minutes. Rinse.

• For defense against a head lice infestation, use daily for at

least 10 to 14 days to kill any lice that may have hatched.

• For an active head lice infestation, use Vamousse® Lice

Treatment before using this shampoo.

Children under 2 years: ask a doctor.

Product may be used as often as needed.

Inactive Ingredients

Inactive Ingredients Benzyl alcohol, Butyl lactate,

Cocamidopropyl betaine, Diazolidinyl urea, Fragrance, Isopropyl

myristate, Sodium chloride, Sodium lauryl s sulfate, Water

Questions?

Questions? 1.855.373.7210 or www.VamousseLice.com

Call to report serious side effects

Additionl Label Content

Manufactured For:

Alliance Pharma Inc., Cary, NC 27511

Made in the U.S.A. Vamousse, Alliance and associated devices are trade

marks of Alliance Pharmaceuticals Limited

VAMOUSSE LICE PREVENTION SHAMPOO 295 ML Bottle

SUPER LICE DEFENSE

NDC 72238-002-01

DAILY DEFENSE AGAINST LICE

LICE DEFENSE

VAMOUSSE®

GENTLE SHAMPOO

Kills Lice*

Safe, Non-Toxic

Pesticide-Free

100%

Satisfaction

Guaranteed

For use by the whole family during

School outbreaks

Summer camp, sleepovers

Treatment of a sibling

100% Satisfaction Guaranteed

*as shown in lab studies

HOMEOPATHIC

10 FL OZ (295 ml)

Drug Facts

Active Ingredients Purpose

Eucalyptus globulus 2X (HPUS) Pediculicide

Natrum muriaticum 2X (HPUS) Pediculicide

Uses: For daily defense against head lice infestations.

Warnings

For external use only.

Do not use • near eyes • inside nose or mouth

• on eyebrows or eyelashes. See a doctor if lice are

present in these areas. Do not use if you have ever had an

allergic reaction to this product or any of its ingredients.

When using this product:

• Do not use in or near the eyes. Close eyes while applying.

• Do not permit contact with mucous membranes, such as

inside the nose, as irritation or stinging may occur.

Stop use and ask a doctor • if eye irritation occurs

• skin or scalp irritation or infection occurs.

If pregnant or breast-feeding, ask a health

professional before use.

Keep out of reach of children. If swallowed, get

medical help or contact a Poison Control Center right away.

Directions:

Adults and children 2 years and older:

• Apply a generous amount of shampoo to wet hair, work

into a lather and massage into scalp. Leave shampoo in

hair for at least 3 minutes. Rinse.

• For defense against a head lice infestation, use daily for at

least 10 to 14 days to kill any lice that may have hatched.

• For an active head lice infestation, use Vamousse® Lice

Treatment before using this shampoo.

Children under 2 years: ask a doctor.

Product may be used as often as needed.

Inactive Ingredients Benzyl alcohol, Butyl lactate,

Cocamidopropyl betaine, Diazolidinyl urea, Fragrance, Isopropyl

myristate, Sodium chloride, Sodium lauryl s sulfate, Water

Questions? 1.855.373.7210 or www.VamousseLice.com

Call to report serious side effects

Manufactured For:

Alliance Pharma Inc., Cary, NC 27518

Made in the U.S.A. Vamousse, Alliance and associated devices are trade

marks of Alliance Pharmaceuticals Limited